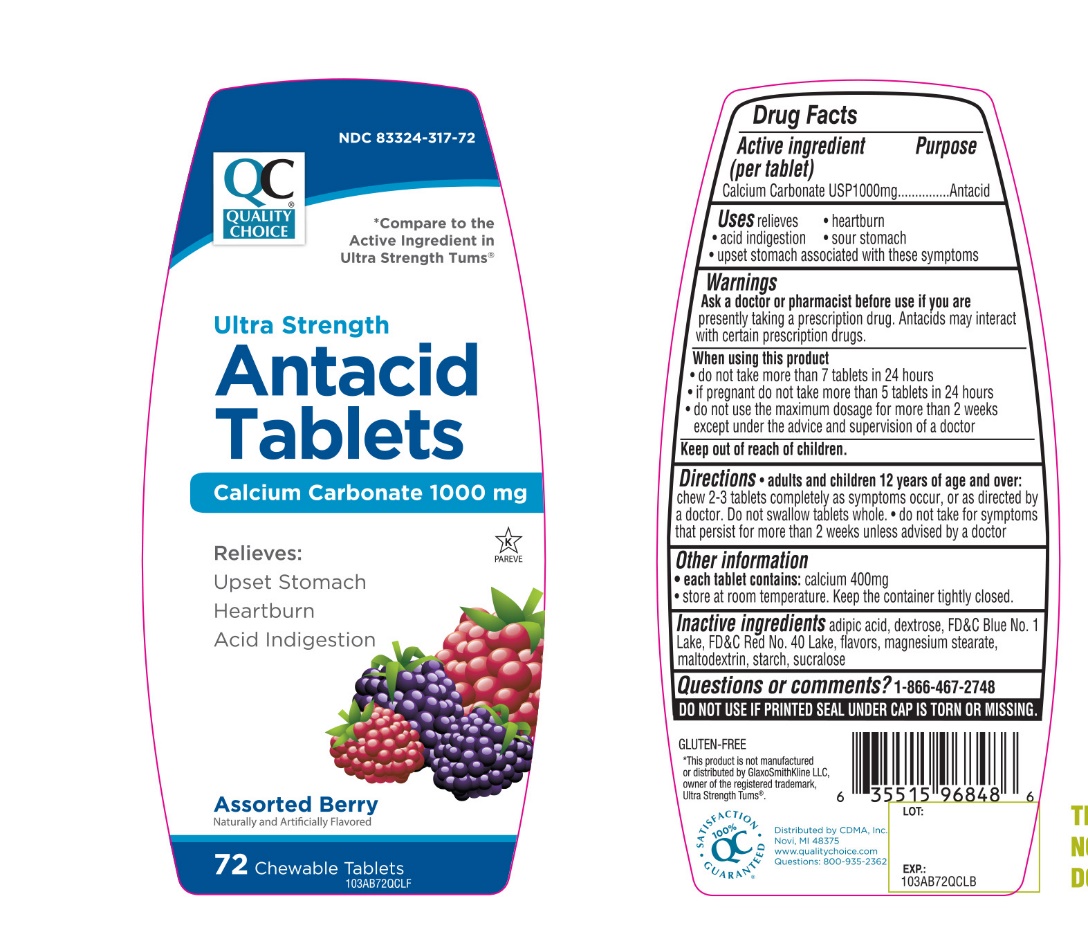 DRUG LABEL: QUALITY CHOICE

NDC: 83324-317 | Form: TABLET, CHEWABLE
Manufacturer: QUALITY CHOICE (Chain drug Marketing Assoiciation)
Category: otc | Type: HUMAN OTC DRUG LABEL
Date: 20251204

ACTIVE INGREDIENTS: CALCIUM CARBONATE 1000 mg/1 1
INACTIVE INGREDIENTS: ADIPIC ACID; FD&C BLUE NO. 1; DEXTROSE, UNSPECIFIED FORM; MAGNESIUM STEARATE; MALTODEXTRIN; FD&C RED NO. 40; STARCH, CORN; SUCRALOSE

Ultra Strength Assorted Berry Antacid Calcium Supplement Drug Facts

Active ingredient (per tablet)

Calcium Carbonate USP 1000mg

Purpose

Antacid

Uses

relieves

- heartburn
- acid indigestion
- sour stomach
- upset stomach associated with these symptoms

Ask a doctor or pharmacist before use if you are

taking a prescription drug. Antacids may interact with certain prescription drugs.

When using this product

- do not take more than 7 tablets in 24 hours
- If pregnant do not take more than 5 tablets in 24 hours
- do not use the maximum dosage for more than 2 weeks except under the advice and supervision of a doctor.

Directions

- adults and children 12 years of age and over: chew 2-3 tablets completely as symptoms occur, or as directed by a doctor
- Do not swallow tablets whole.
- Do not take for symptoms that persist for more than 2 weeks unless advised by a doctor.

Other Information

- Each tablet contains: calcium 400mg
- Store at room temperature.Keep the container tightly closed

Safety sealed: Do not use if printed seal under cap is torn or missing.

Inactive ingredients

adipic acid, dextrose, FD&C Blue No.1 lake, Red No.40 lake, flavors, magnesium stearate, maltodextrin, starch, sucralose.

Questions or comments?

1-866-467-2748

Package/Label Principal Display Panel

* Compare to the active ingredient in Ultra Strength Tums®

QUALITY CHOICE®

NDC# 83324-317-72

Ultra Strength

Antacid Tablets

Calcium Carbonate 1000 mg

Relieves:

- Upset Stomach
- Heartburn
- Acid Indigestion

Assorted Berry

Naturally and Artificially Flavored

GLUTEN FREE

72 CHEWABLE TABLETS

K PAREVE

QC SATISFACTION GURANTEED

Distributed by: C.D.M.A., Inc.

Novi, MI 48376-0995

www.qualitychoice.com

Questions: 800-935-2362

*This product is not manufactured or distributed by GlaxoSmithKline, the owner of the registered trademark, Ultra Strength Tums®.